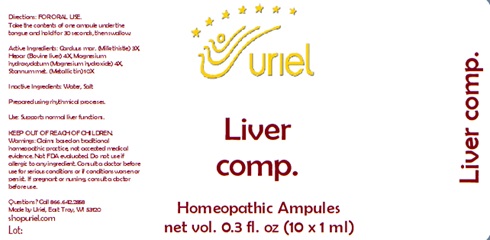 DRUG LABEL: Liver comp.
NDC: 48951-6044 | Form: LIQUID
Manufacturer: Uriel Pharmacy Inc.
Category: homeopathic | Type: HUMAN OTC DRUG LABEL
Date: 20241202

ACTIVE INGREDIENTS: MILK THISTLE 3 [hp_X]/1 mL; MAMMAL LIVER 4 [hp_X]/1 mL; MAGNESIUM CATION 4 [hp_X]/1 mL; TIN 10 [hp_X]/1 mL
INACTIVE INGREDIENTS: WATER; SODIUM CHLORIDE

Liver comp.

INDICATIONS AND USAGE

Directions: FOR ORAL USE.

DOSAGE AND ADMINISTRATION

Take the contents of one ampule under the tongue and hold for 30 seconds, then swallow.

ACTIVE INGREDIENT

Active Ingredients: Carduus mar. (Milk thistle) 3X, Hepar (Bovine liver) 4X, Magnesium hydroxydatum (Magnesium hydroxide) 4X, Stannum met. (Metallic tin) 10X

Inactive Ingredients: Water, Salt

Prepared using rhythmical processes.

PURPOSE

Use: Supports normal liver functions.

KEEP OUT OF REACH OF CHILDREN.

WARNINGS

Warnings: Claims based on traditional homeopathic practice, not accepted medical evidence. Not FDA evaluated. Do not use if allergic to any ingredient. Consult a doctor before use for serious conditions or if conditions worsen or persist. If pregnant or nursing, consult a doctor before use.

Questions? Call 866.642.2858
Made by Uriel, East Troy, WI 53120
shopuriel.com Lot;